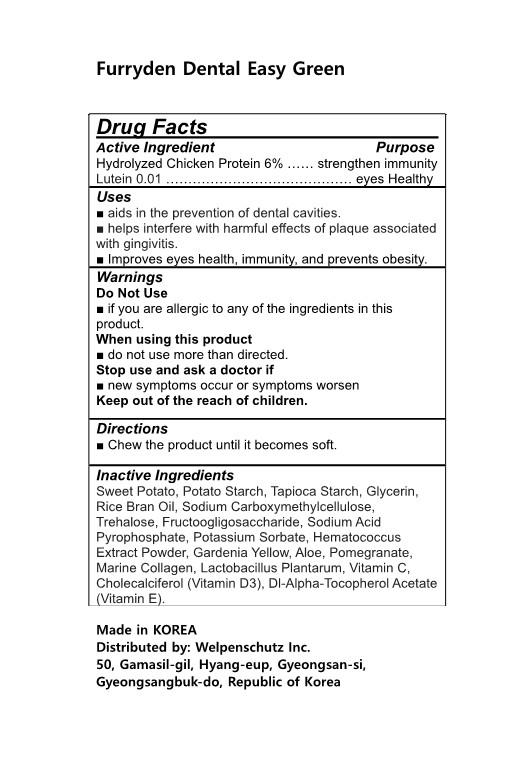 DRUG LABEL: Furryden Dental Easy Green
NDC: 83332-401 | Form: GUM, CHEWING
Manufacturer: Welpenschutz Inc.
Category: otc | Type: HUMAN OTC DRUG LABEL
Date: 20230209

ACTIVE INGREDIENTS: LUTEIN 0.01 g/100 mL; CHICKEN 6 g/100 mL
INACTIVE INGREDIENTS: GLYCERIN; FRUCTOSE; SWEET POTATO; TREHALOSE; ALOE; RICE BRAN OIL; SODIUM ACID PYROPHOSPHATE; .ALPHA.-TOCOPHEROL ACETATE, DL-; STARCH, POTATO; CARBOXYMETHYLCELLULOSE SODIUM; CHOLECALCIFEROL; POTASSIUM SORBATE; GARDENIA YELLOW; POMEGRANATE; STARCH, TAPIOCA; LACTIPLANTIBACILLUS PLANTARUM; ASCORBIC ACID; HAEMATOCOCCUS PLUVIALIS

83332-401 Furryden Dental Easy Green

Active Ingredients

Hydrolyzed Chicken Protein 6%

Lutein 0.01

Purposes

Hydrolyzed Chicken Protein 6% …… strengthen immunity

Lutein 0.01 …………………………………… eyes Healthy

Uses

■ aids in the prevention of dental cavities.

■ helps interfere with harmful effects of plaque associated with gingivitis.

■ Improves eyes health, immunity, and prevents obesity.

Warnings

Do Not Use

■ if you are allergic to any of the ingredients in this product.

When using this product

■ do not use more than directed.

Stop use and ask a doctor if

■ new symptoms occur or symptoms worsen

Keep out of the reach of children.

Warnings

When using this product

■ do not use more than directed.

Warnings

Stop use and ask a doctor if

■ new symptoms occur or symptoms worsen

Warnings

Keep out of the reach of children.

Warnings

Do Not Use

■ if you are allergic to any of the ingredients in this product.

Inactive Ingredients

Sweet Potato, Potato Starch, Tapioca Starch, Glycerin, Rice Bran Oil, Sodium Carboxymethylcellulose, Trehalose, Fructoogligosaccharide, Sodium Acid Pyrophosphate, Potassium Sorbate, Hematococcus Extract Powder, Gardenia Yellow, Pomegranate, Marine Collagen, Lactobacillus Plantarum, Vitamin C, Cholecalciferol (Vitamin D3), Dl-Alpha-Tocopherol Acetate (Vitamin E).

Directions

■ Chew the product until it becomes soft.